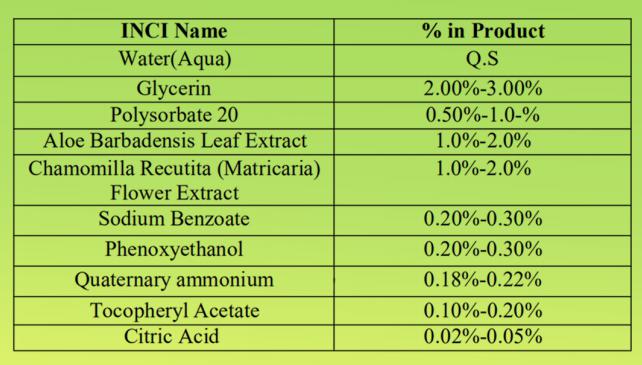 DRUG LABEL: WET WIPES
NDC: 78936-002 | Form: SWAB
Manufacturer: Hangzhou Caring Cleaning Commodity Co.,Ltd
Category: otc | Type: HUMAN OTC DRUG LABEL
Date: 20200617

ACTIVE INGREDIENTS: GLYCERIN 3 g/100 g; PHENOXYETHANOL 0.3 g/100 g
INACTIVE INGREDIENTS: CITRIC ACID ACETATE; POLYSORBATE 20; CHAMOMILE; ALOE VERA LEAF; ALPHA-TOCOPHEROL ACETATE; WATER; COCAMIDOPROPYL HYDROXYSULTAINE

WET WIPES

Active Ingredient(s)

Quaternary ammonium, Phenoxyethanol

Purpose

Antiseptic

Use

Decreases bacteria on skin. Recommended for repeated use

Warnings

For external use only. Flammable, keep product away from fire or flame.

Do not use over large areas of the body if you are allergic to any of the ingredients when using this product,avoid contact with eyes and face.If contact occurs,flush thoroughly with water.Stop use and ask a doctor if irritation or rash develops and continues for more than 72 hours.

Do not use

- in children less than 2 months of age
- on open skin wounds

Stop use and ask a doctor if irritation or rash occurs. These may be signs of a serious condition.

Stop use and ask a doctor if irritation or rash occurs. These may be signs of a serious condition.

Keep out of reach of children. If swallowed, get medical help or contact a Poison Control Center right away.

Inactive ingredients

Water,Glycerin，Polysorbate 20，Aloe Barbadensis Leaf Extract，Chamomilla Recutita (Matricaria) Flower Extract，Tocopheryl Acetate，Citric Acid

Directions

For adults and children of 2 years and over.children under 2 years ask a doctor before use.

Wet hands thoroughly with product and allow to dry without wiping.

Package Label - Principal Display Panel

100 PCS IN 1 PAIL NDC: 78936-002-01